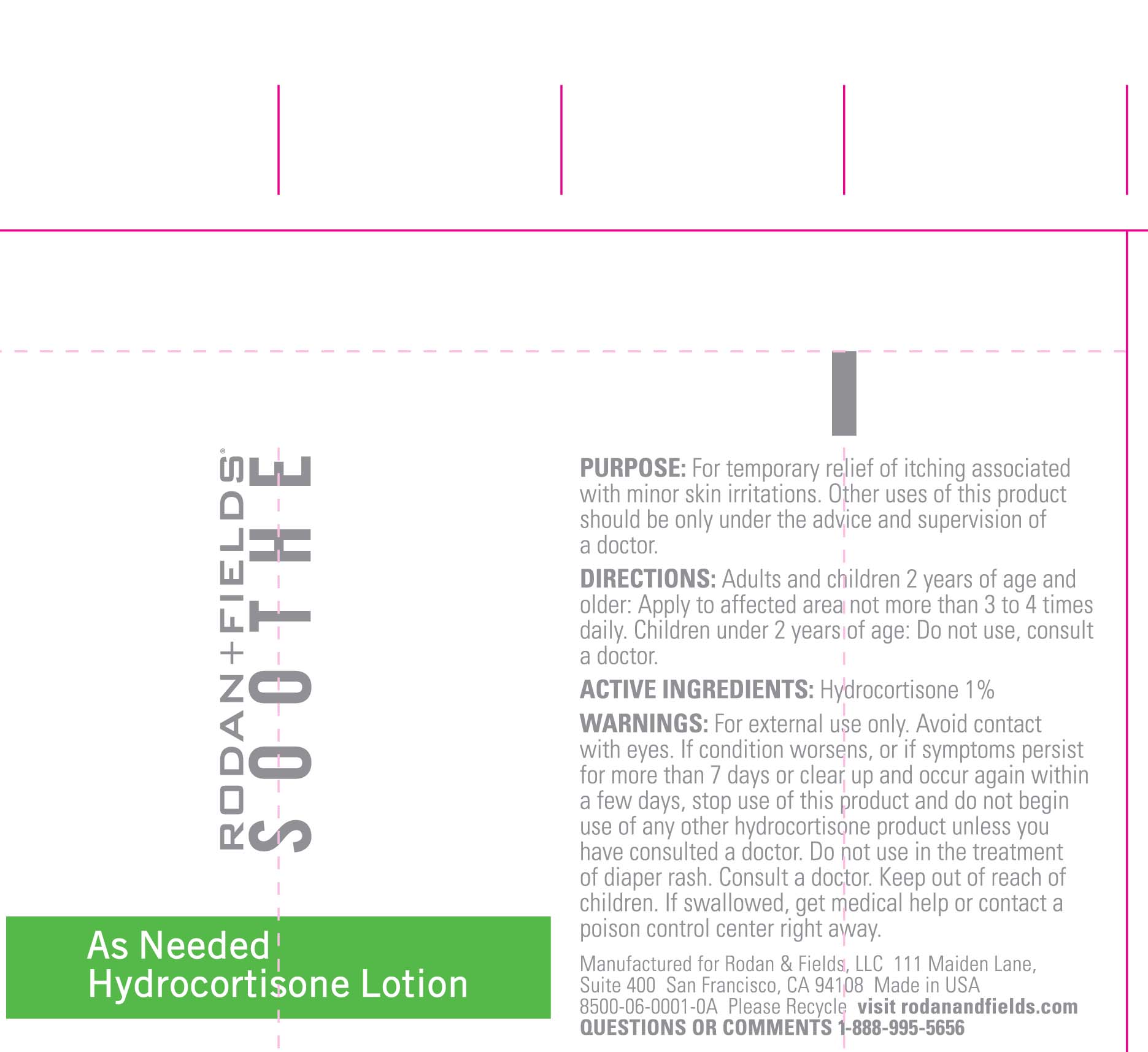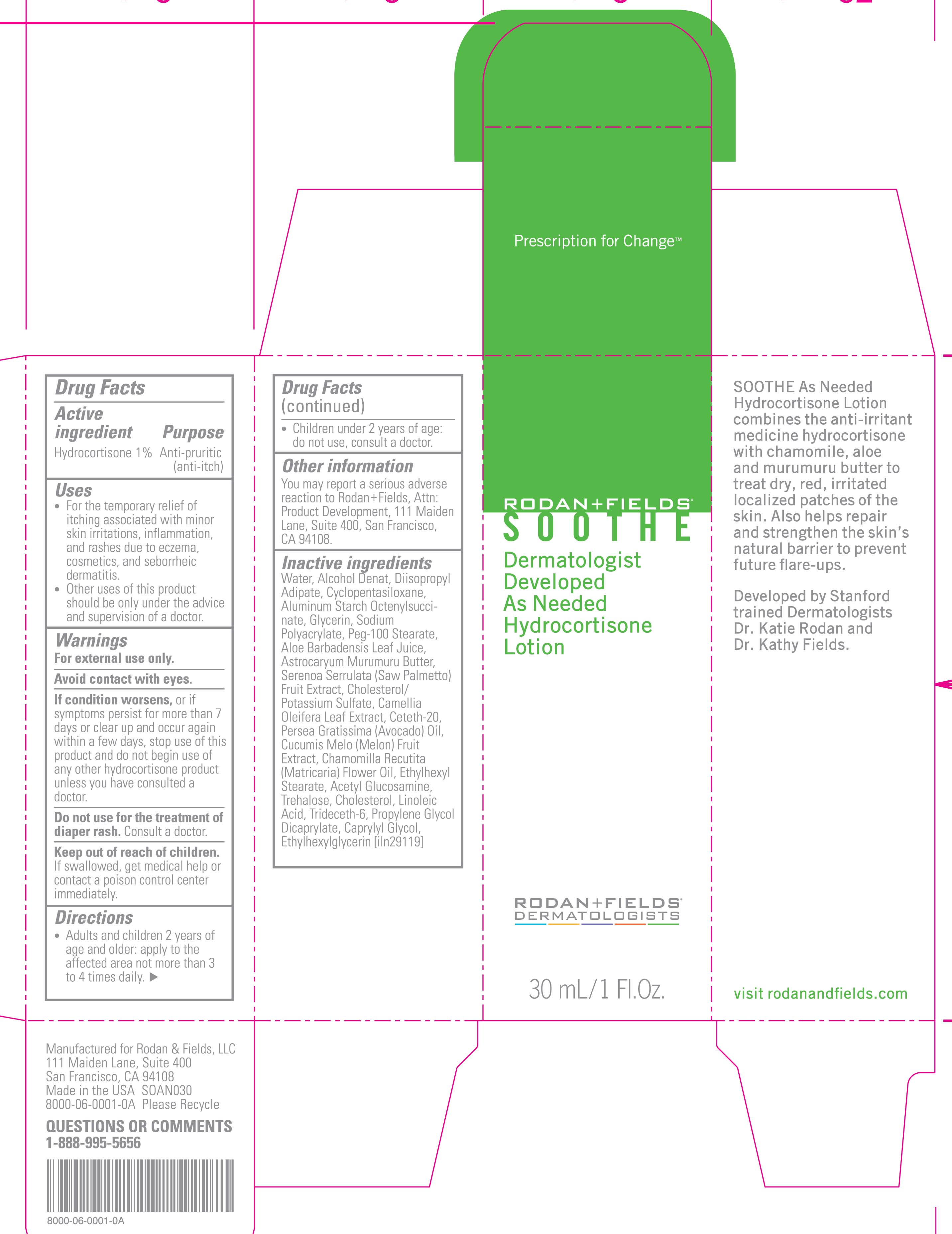 DRUG LABEL: Soothe
NDC: 14222-2003 | Form: LOTION
Manufacturer: Rodan & Fields, LLC. 
Category: otc | Type: HUMAN OTC DRUG LABEL
Date: 20120124

ACTIVE INGREDIENTS: HYDROCORTISONE 1 mL/100 mL
INACTIVE INGREDIENTS: DIISOPROPYL ADIPATE; CYCLOMETHICONE 5; ALUMINUM STARCH OCTENYLSUCCINATE; GLYCERIN; PEG-100 STEARATE; ALOE VERA LEAF; SAW PALMETTO; CAMELLIA OLEIFERA LEAF; CETETH-20; AVOCADO OIL; CHAMOMILE FLOWER OIL; ETHYLHEXYL STEARATE; N-ACETYLGLUCOSAMINE; TREHALOSE; CHOLESTEROL; LINOLEIC ACID; TRIDECETH-6; PROPYLENE GLYCOL DICAPRYLATE; CAPRYLYL GLYCOL; ETHYLHEXYLGLYCERIN

Rodan And Fields Hydrocortisone Lotion

ACTIVE INGREDIENT

HYDROCORTISONE 1%

PURPOSE

Anti- Pruritic (Anti- Itch)

Keep out of reach of children.

if swallowed, get medical help or contact a poison control center immediately.

INDICATIONS AND USAGE

for external use only.

DOSAGE AND ADMINISTRATION

adults and children 2 years of age and older: apply to the effected area not more than 3 to 4 times daily.

children under 2 years of age: do not use, consult a doctor.

WARNINGS

avoid contact with eyes.
if conditions worsens, or if symptoms persist for more than 7 days or clear up and occur again within a few days, stop use of this product and do not begin use of any other hydrocortisone product unless you have consulted a doctor.

INACTIVE INGREDIENT

Water, Alcohol Denat, Diisopropyl Adipate, Cyclopentasiloxane, Aluminum Starch Octenylsuccinate, Glycerin, Sodim Polyacrylate, Peg-100 Stearate, Aloe Barbadensis Leaf Juice, Astrocaryum Murumuru Butter, Serenoa Serrulata (Saw Palmetto) Fruit Extract, Cholesterol/ Potassium Sulfate, Camellia Oleifera Leaf Extract, Ceteth-20, Persea Gratissima (Avocado) Oil, Cucumis Melo (Melon) Fruit Extract, Chamomilla Recutita (Matricaria) Flower Oil, Ethylhexyl Stearate, Acetyl Glucosamine, Trehalose, Cholesterol, Linoleic Acid, Trideceth-6, Propylene Glycol, Dicaprylate, Caprylyl Glycol, Ethylhexylglycerin

PACKAGE LABEL

Rodan and Fields

Soothe

Dermatologist Developed as needed

Hydrocortisone Lotion

30 mL/ 1 Fl. Oz.